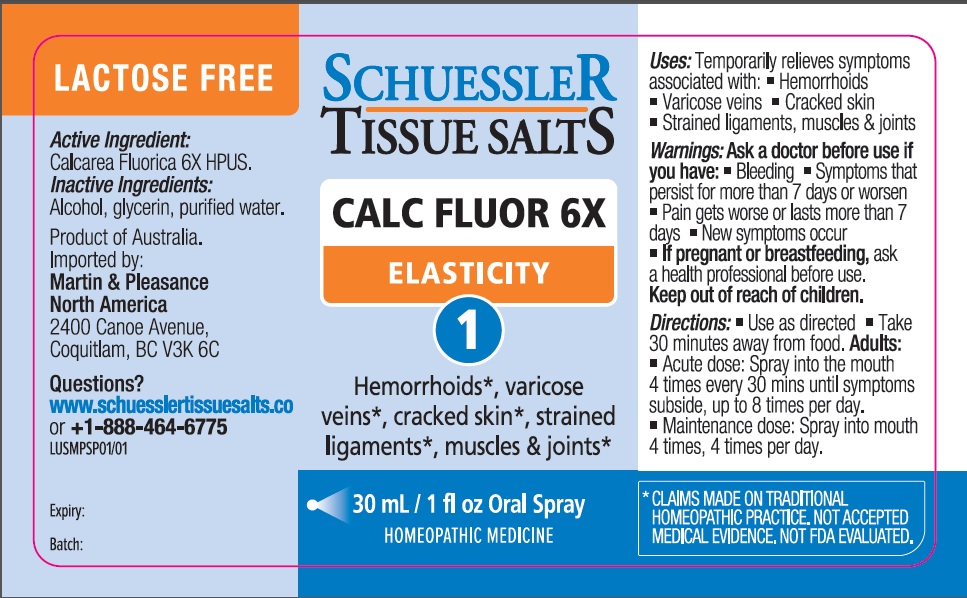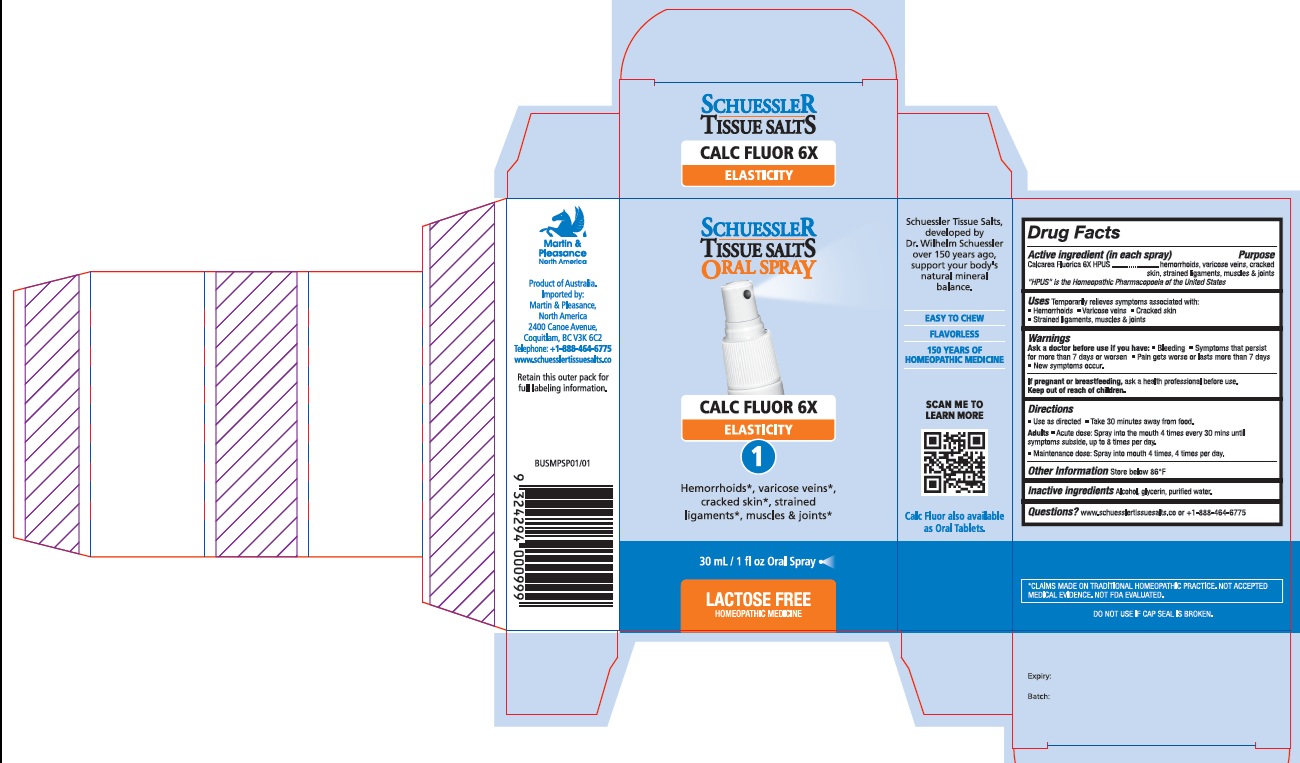 DRUG LABEL: Schuessler Tissue Salts Calc Fluor Elasticity 1
NDC: 84999-001 | Form: SPRAY
Manufacturer: Martin & Pleasance Pty Ltd
Category: homeopathic | Type: HUMAN OTC DRUG LABEL
Date: 20250701

ACTIVE INGREDIENTS: CALCIUM FLUORIDE 6 [hp_X]/30 mL
INACTIVE INGREDIENTS: ALCOHOL; GLYCERIN; WATER

Active Ingredients Purpose

Calcarea fluorica 6X HPUS hemorrhoids, varicose veins, cracked skin, strained ligaments, muscles & joints

" HPUS" is the Homeopathic Pharmacopoeia of the United States

Uses

Temporarily relieves symptoms associated with: Hemorrhoids Varicose veins Cracked skin Strained ligaments, muscles and joints

Warnings

Ask a doctor before use if you have:

- Bleeding
- Symptoms lhat persist for more than 7 days or worsen
- Pain gets worse or lasts more than 7 days
- New symptoms occur.

If pregnant or breastfeeding, ask a health professional before use. Keep out of reach of children.

Directions

- Use as directed
- Take 30 minutes away from food.

Adults• Acute dose: Spray into the mouth 4 times every 30 mins until symptoms subside, up to 8 times per day.
• Maintenance dose: Spray into mouth 4 times, 4 times per day.

Other Information

Store below 86°F

Inactive Ingredients

Alcohol, glycerin, purified water.

Questions?www.schuesslertissuesalts.co or + 1-888-464-6775